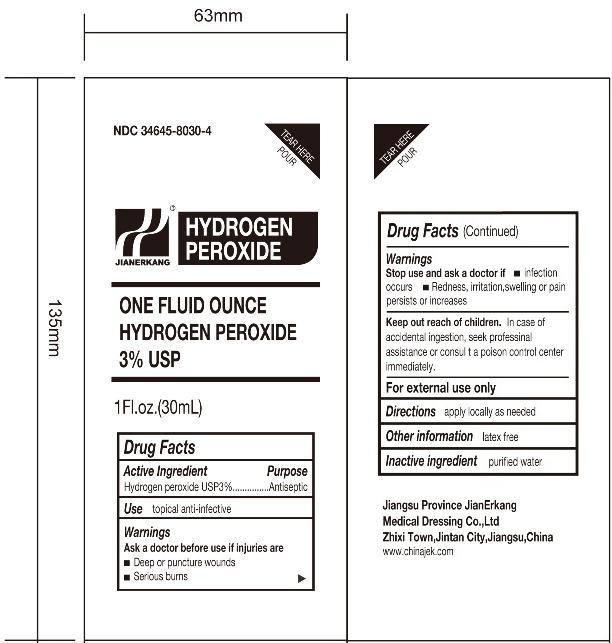 DRUG LABEL: Hydrogen Peroxide
NDC: 34645-8030 | Form: SOLUTION
Manufacturer: Jiangsu Province JianErKang Medical Dressing Co. ,Ltd.
Category: otc | Type: HUMAN OTC DRUG LABEL
Date: 20100501

ACTIVE INGREDIENTS: HYDROGEN PEROXIDE 0.03 mL/1 mL

Drug Facts

Active Ingredients

Hydrogen Peroxide 3% USP

Purpose

Antiseptic

Use

Topical Anti-Infective

Warnings

Ask a doctor before use if injures are

Deep or puncture wounds

Serious Burns

Stop Use and Ask a doctor if

infection occurs

redness, irritation, swelling or pain persists or increase

Keep out of reach of children

In case of accidental ingestion, seek professional assistance or consult a Poison Control Center immediately

INDICATIONS AND USAGE

For External Use Only

Directions

Apply locally as needed

Other Information

Latex Free

Inactive Ingredient

purified water

Image of Pouch Label